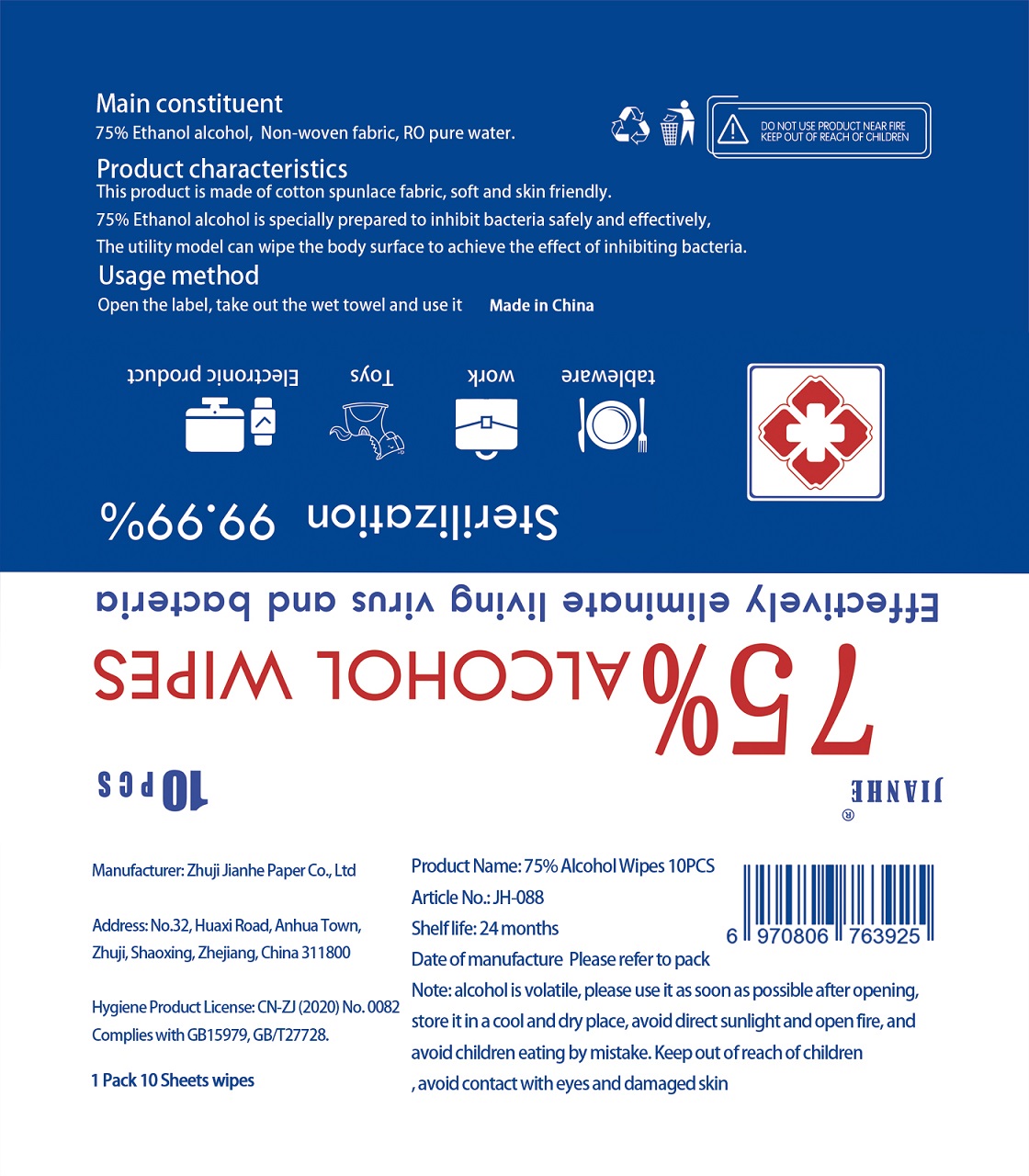 DRUG LABEL: 75% Alcohol Wipes
NDC: 75163-100 | Form: PATCH
Manufacturer: Zhuji Jianhe Paper Co., Ltd
Category: otc | Type: HUMAN OTC DRUG LABEL
Date: 20200519

ACTIVE INGREDIENTS: ALCOHOL 0.75 U/1 U
INACTIVE INGREDIENTS: WATER

JianHe, 75% Alcohol Wipes, *10

Active ingredient

Ethanol Alcohol, 75% v/v, antiseptic

Inactive ingredient

Water

Purpose

Daily Clean for daily items and Antimicrobial.

When using

This product is used to wipe hands, faces, skins, etc. It can also be used to clean many kinds of places.

Do not use

- on children less than 2 months of age
- on open skin wounds

Stop use

if irritation or rash occurs.

These may be signs of a serious condition.

Keep out of reach of children

Indications & usage

This product is used to wipe hands, faces, skins, etc. It can also be used to clean many kinds of places.

Open the label, take out the wet towel and wipe the target area.

Dosage & administration

Use it as needed, after following the usage instructions.

For external use only.

Warnings

Do not apply this product to red and swollen skin, wound or any part sensitive to it.

Keep this product out of children’s reach in case they might eat it.
Alcohol is violatile, please use it as soon as possible after opening, store it in a cool and dry place, avoid direct sunlight and open fire, and avoid contact with eyes and damaged skin.